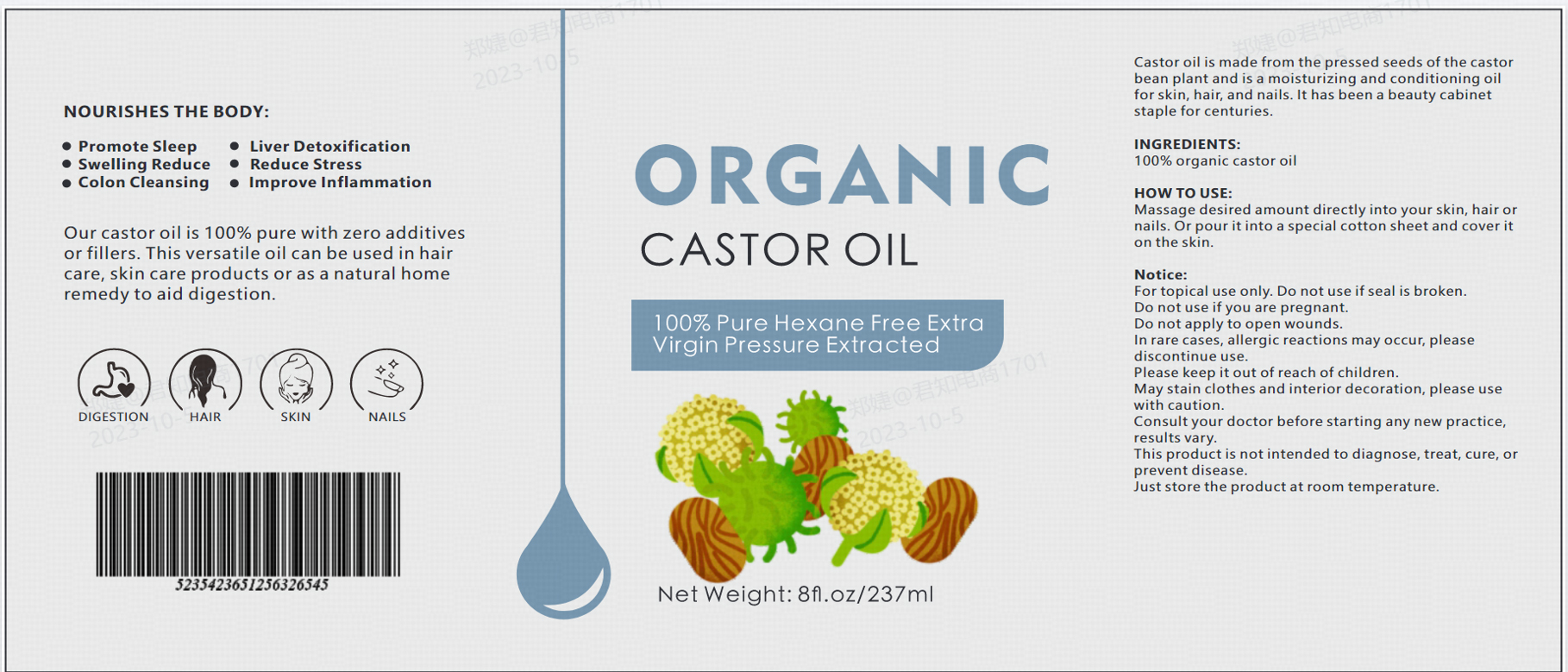 DRUG LABEL: Castor oil
NDC: 83788-101 | Form: LIQUID
Manufacturer: Xiamen Panmai Technology Co., Ltd
Category: otc | Type: HUMAN OTC DRUG LABEL
Date: 20231225

ACTIVE INGREDIENTS: CASTOR OIL 1000 mg/1 mL

Castor oil

Castor oil

ACTIVE INGREDIENT

Castor oil 100%

PURPOSE

Our castor oil is 100% pure with zero additivesor fillers. This versatile oil can be used in haircare, skin care products or as a natural homeremedy to aid digestion.

INDICATIONS AND USAGE

Promote Sleep

Liver Detoxification

Swelling Reduce

Reduce Stress

Colon Cleansing

Improve Inflammation

WARNINGS

For topical use only. Do not use if seal is broken.

Do not use if you are pregnant.

Do not apply to open wounds.

DO NOT USE

For topical use only. Do not use if seal is broken.

Do not use if you are pregnant.

Do not apply to open wounds.

WHEN USING

Consult your doctor before starting any new practice,results vary.This product is not intended to diagnose, treat, cure, orprevent disease.

STOP USE

In rare cases, allergic reactions may occur, please discontinue use.

Please keep it out of reach of children.

DOSAGE AND ADMINISTRATION

Massage desired amount directly into your skin, hair ornails. Or pour it into a special cotton sheet and cover iton the skin.

STORAGE AND HANDLING

Just store the product at room temperature.

INACTIVE INGREDIENT

none